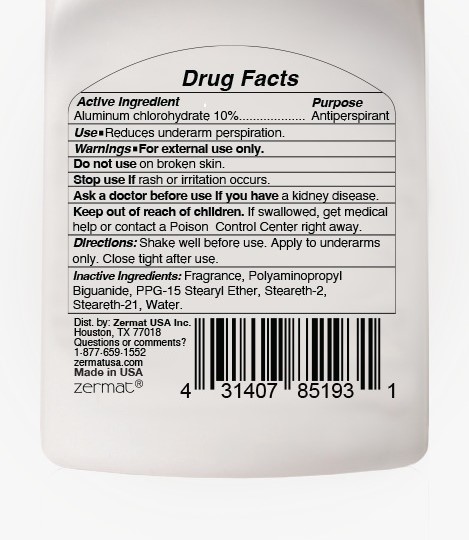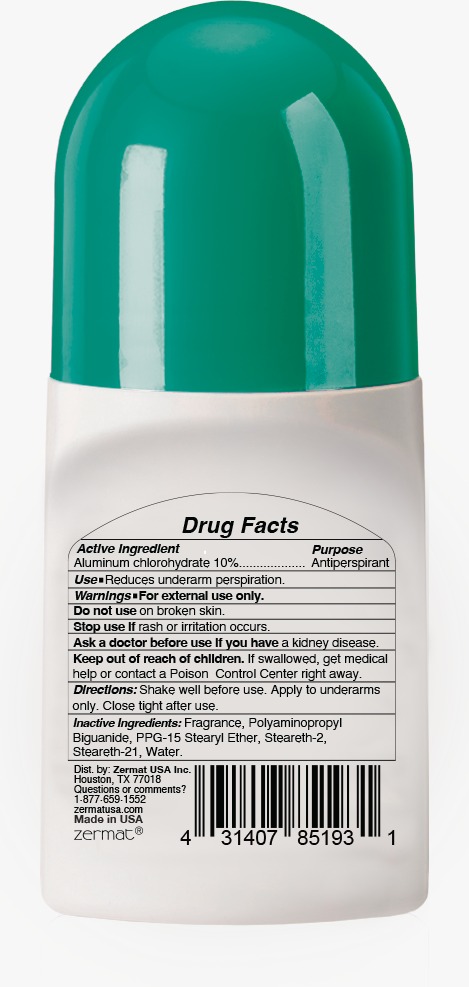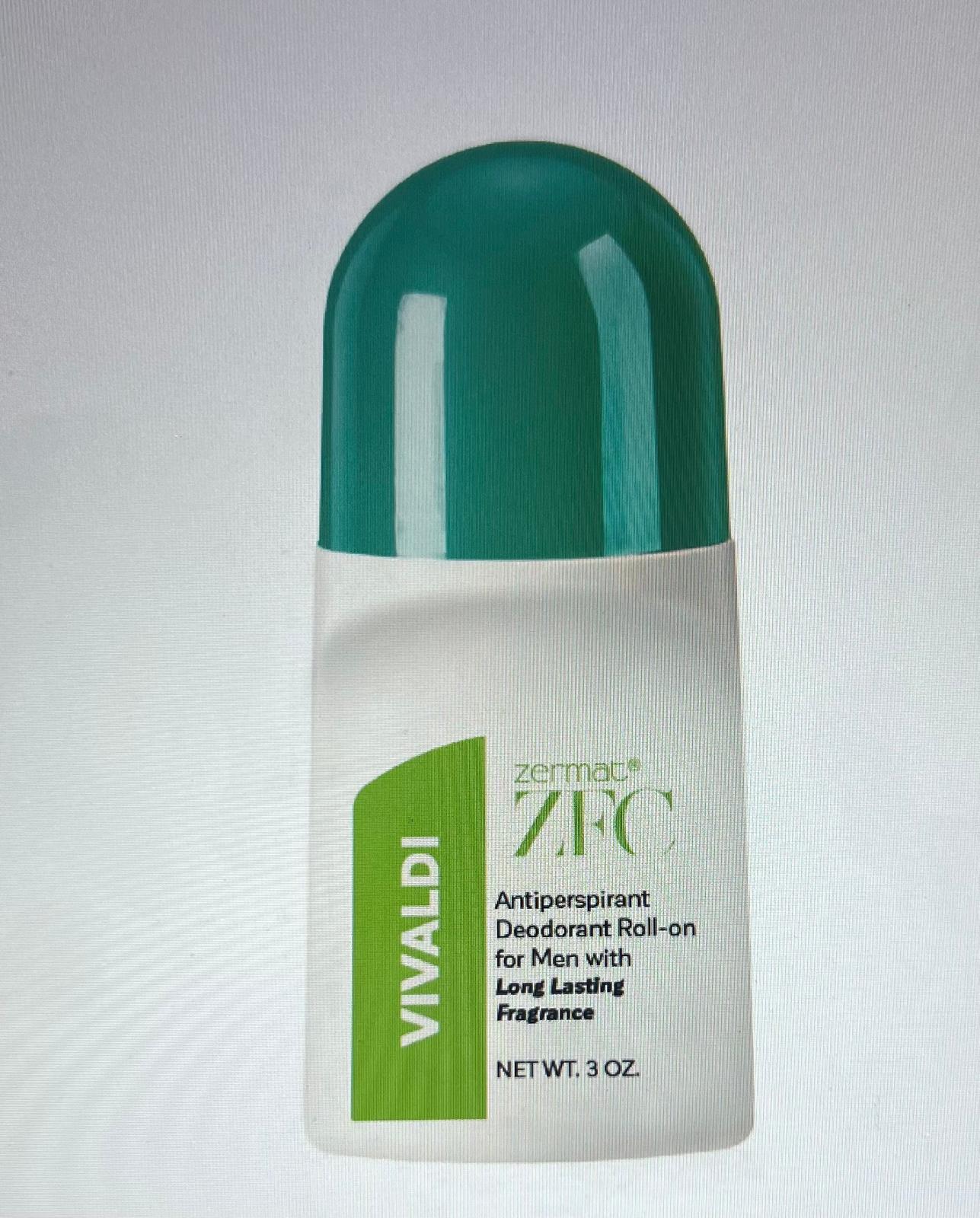 DRUG LABEL: VIVALDI ANTIPERSPIRANTDEODORANT ROLL-ON FOR MEN
NDC: 84178-032 | Form: CREAM
Manufacturer: EVI LABS
Category: otc | Type: HUMAN OTC DRUG LABEL
Date: 20260116

ACTIVE INGREDIENTS: ALUMINUM CHLOROHYDRATE 8.5 g/85 g
INACTIVE INGREDIENTS: STEARETH-2 3.4 g/85 g; POLYAMINOPROPYL BIGUANIDE 0.17 g/85 g; WATER 66.343 g/85 g; STEARETH-21 1.913 g/85 g; FRAGRANCE CLEAN ORC0600327 1.5 g/85 g; PPG-15 STEARYL ETHER 3.4 g/85 g

VIVALDI ANTIPERSPIRANT DEODORANT ROLL-ON FOR MEN

Active Ingredients

ALUMINUM CHLOROHYDRATE 10%

PURPOSE

ATIPERSPIRANT

USE

REDUCES UNDERARM PERSPIRATION.

WARNING

FOR EXTERNAL USE ONLY

INSTRUCTION FOR USES

DO NOT USE ON BROKEN SKIN.

STOP USE IF RASH OR IRRITATION OCCURS

INACTIVE INGREDIENTS

Fragrance, Poly aminopropyl Biguanide, PPG-15 Stearyl Ether, Steareth-2, Steareth-21, Water.

DIRECTIONS

SHAKE WELL BEFORE USE. APPLY TO UNDERARMS ONLY. CLOSE TIGHT AFTER USE.

DOSAGE & ADMINISTRATION

APPLY TO UNDERARMS ONLY

KEEP OUT OF REACH OF CHILDREN

IF SWALLOWED, GET MEDICAL HELP OR CONTACT A POISON CONTROL CENTER RIGHT AWAY.